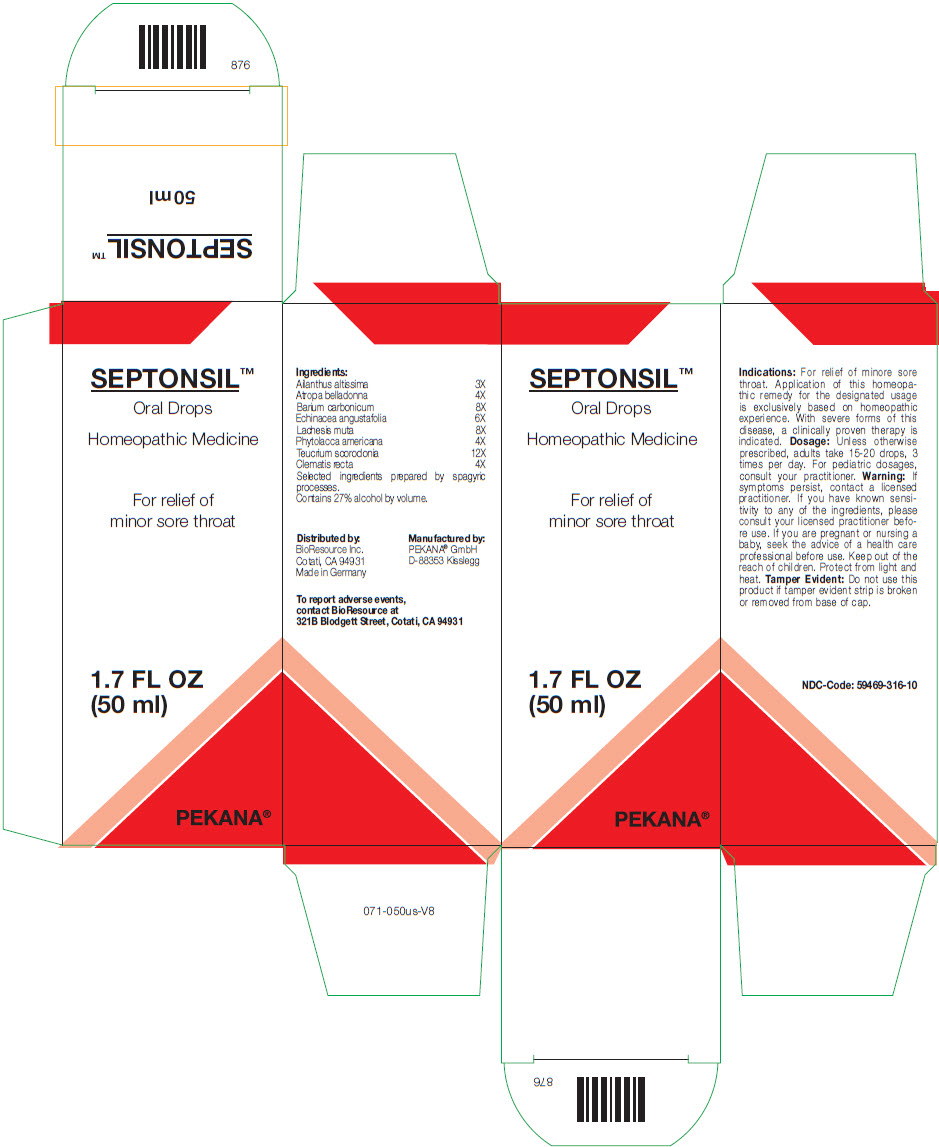 DRUG LABEL: SEPTONSIL
NDC: 59469-316 | Form: SOLUTION/ DROPS
Manufacturer: PEKANA Naturheilmittel GmbH
Category: homeopathic | Type: HUMAN OTC DRUG LABEL
Date: 20230111

ACTIVE INGREDIENTS: AILANTHUS ALTISSIMA WHOLE 3 [hp_X]/50 mL; ATROPA BELLA-DONNA FLOWERING TOP 4 [hp_X]/50 mL; BARIUM CARBONATE 8 [hp_X]/50 mL; LACHESIS MUTA VENOM 8 [hp_X]/50 mL; PHYTOLACCA AMERICANA ROOT 4 [hp_X]/50 mL; CLEMATIS RECTA FLOWERING TOP 4 [hp_X]/50 mL; ECHINACEA, UNSPECIFIED 6 [hp_X]/50 mL; TEUCRIUM SCORODONIA FLOWERING TOP 12 [hp_X]/50 mL
INACTIVE INGREDIENTS: WATER; ALCOHOL

SEPTONSIL™

ACTIVE INGREDIENT

Ingredients:
Ailanthus altissima | 3X
Atropa belladonna | 4X
Barium carbonicum | 8X
Echinacea angustafolia | 6X
Lachesis muta | 8X
Phytolacca americana | 4X
Teucrium scorodonia | 12X
Clematis recta | 4X

Selected ingredients prepared by spagyric processes.

INACTIVE INGREDIENT

Contains 27% alcohol by volume.

Indications

PURPOSE

For relief of minore sore throat. Application of this homeopathic remedy for the designated usage is exclusively based on homeopathic experience. With severe forms of this disease, a clinically proven therapy is indicated.

Dosage

Unless otherwise prescribed, adults take 15-20 drops, 3 times per day. For pediatric dosages, consult your practitioner.

Warning

If symptoms persist, contact a licensed practitioner. If you have known sensitivity to any of the ingredients, please consult your licensed practitioner before use. If you are pregnant or nursing a baby, seek the advice of a health care professional before use.

Keep out of the reach of children.

STORAGE AND HANDLING

Protect from light and heat.

Tamper Evident

Do not use this product if tamper evident strip is broken or removed from base of cap.

QUESTIONS

To report adverse events, contact BioResource at 321B Blodgett Street, Cotati, CA 94931

Distributed by:
BioResource Inc.
Cotati, CA 94931

Manufactured by:
PEKANA® GmbH
D-88353 Kisslegg

PRINCIPAL DISPLAY PANEL - 50 ml Bottle Box

SEPTONSIL™

Oral Drops

Homeopathic Medicine

For relief of
minor sore throat

1.7 FL OZ
(50 ml)

PEKANA®